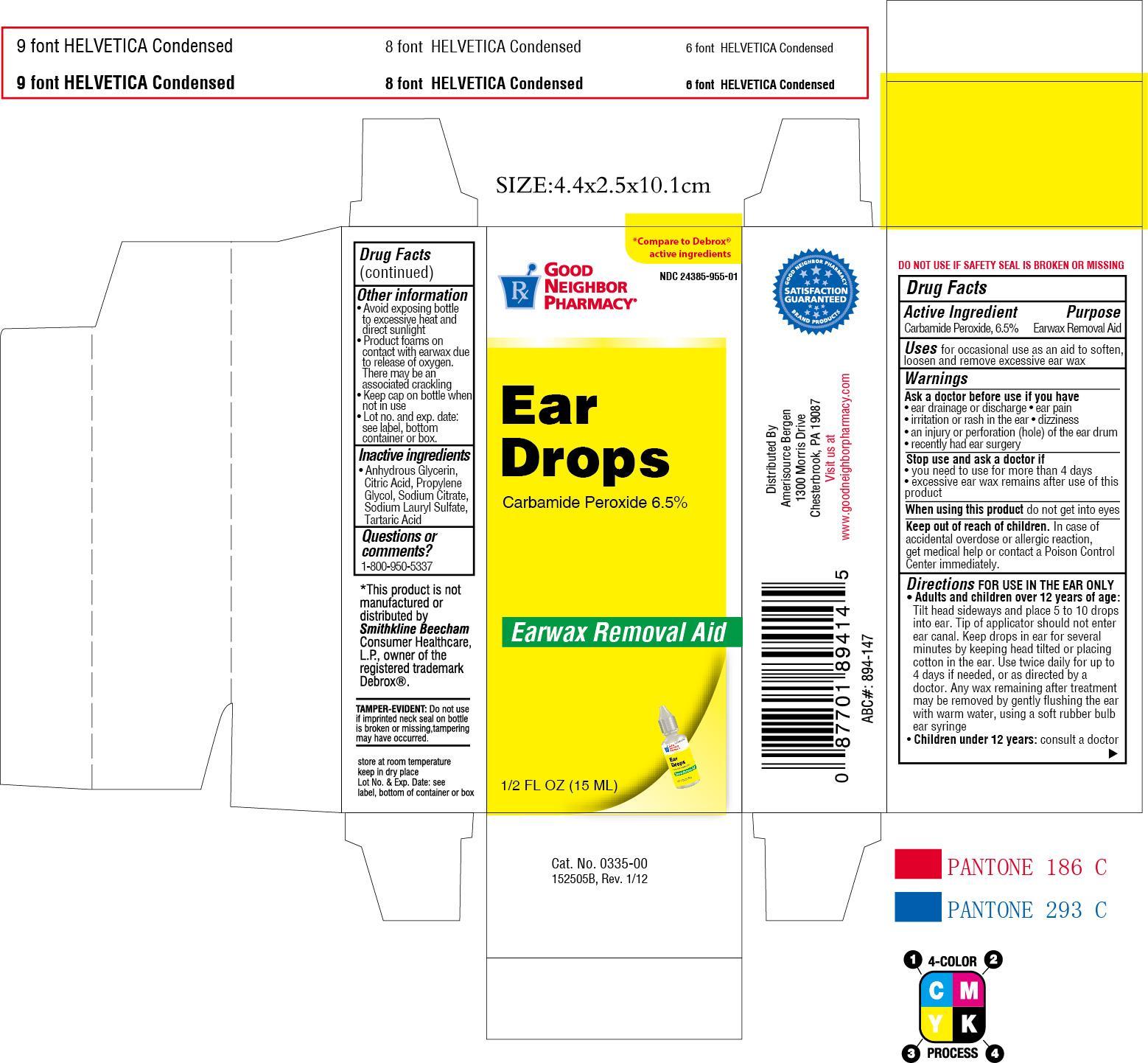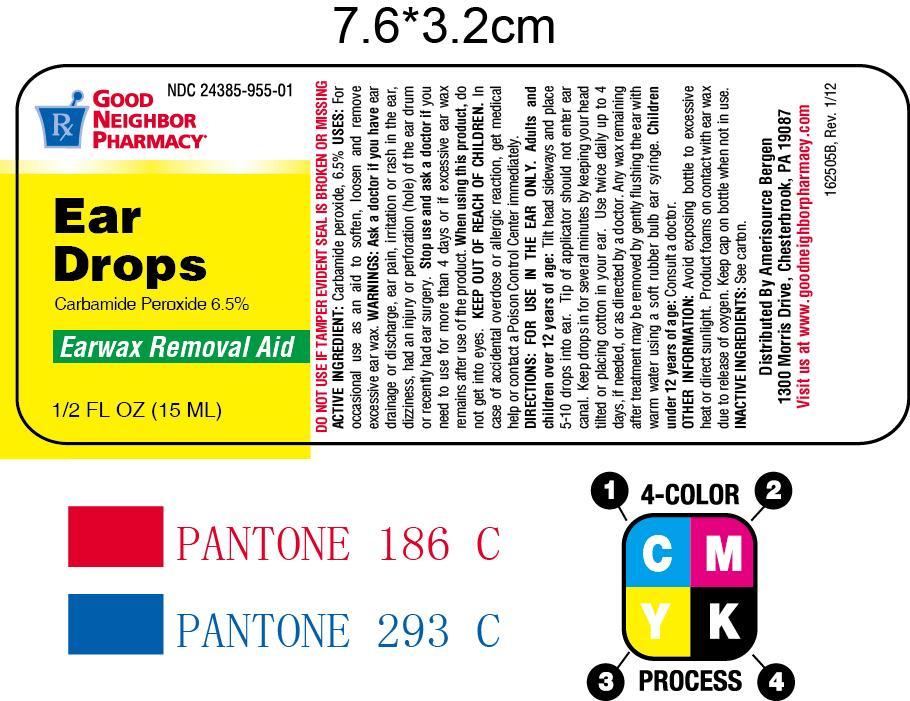 DRUG LABEL: Ear Drops
NDC: 24385-955 | Form: LIQUID
Manufacturer: AmerisourceBergen Drug Corporation (Good Neighbor Pharmacy)
Category: otc | Type: HUMAN OTC DRUG LABEL
Date: 20130628

ACTIVE INGREDIENTS: CARBAMIDE PEROXIDE 65 mg/1 mL
INACTIVE INGREDIENTS: GLYCERIN; ANHYDROUS CITRIC ACID; PROPYLENE GLYCOL; SODIUM CITRATE; SODIUM LAURYL SULFATE; TARTARIC ACID

Drug Facts

Active ingredient

Carbamide Peroxide, 6.5%

Purpose

Earwax removal aid

Uses

For occasional use as an aid to soften, loosen and remove excessive ear wax.

Ask a doctor before use if you have

- ear drainage or discharge
- ear pain
- irritation or rash in the ear
- dizziness
- and injury or perforation (hole) of the ear drum
- recently had ear surgery

Stop use and ask a doctor if

- you need to use of r more than 4 days
- excessive ear wax remains after use of this product

When using this product do not get into eyes

Keep out of reach of children

In case of accidental overdose or allergic reaction, get medical help or contact a Poison Control Center immediately

Directions

FOR USE IN THE EAR ONLY

- Adults and children over 12 years of age: Tilt head sideways and place 5 to 10 drops into ear. Tip of applicator should not enter ear canal. Keep drops in ear for several minutes by keeping head tilted or placing cotton in the ear. Use twice daily for up to 4 days if needed, or as directed by a doctor. Any wax remaining after treatment may be removed by gently flushing the ear with warm water, using a soft rubber bulb ear syringe.
- Children under 12 years: consult a doctor.

Other information

- Avoid exposing bottle to excessive heat and direct sunlight.
- Product foams on contact with earwax due to release of oxygen. There may be an associated crackling.
- Keep cap on bottle when not in use.
- Lot no. and exp. date: see label, bottom container or box.

Inactive ingredients

Anhydrous Glycerin, Citric Acid, Propylene Glycol, Sodium Citrate, Sodium Lauryl Sulfate, Tartaric Acid